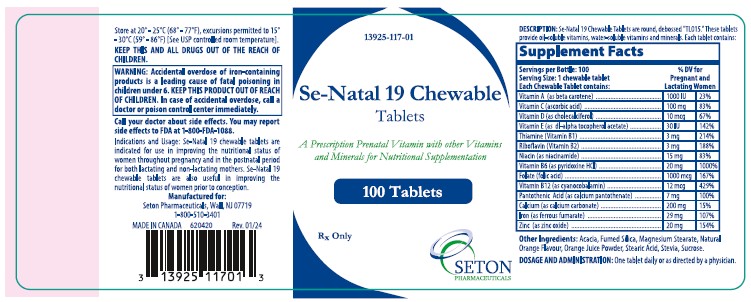 DRUG LABEL: Se-Natal 19 Chewable
NDC: 13925-117 | Form: TABLET, CHEWABLE
Manufacturer: Seton Pharmaceuticals
Category: prescription | Type: HUMAN PRESCRIPTION DRUG LABEL
Date: 20250312

ACTIVE INGREDIENTS: FOLIC ACID 1 mg/1 1; .BETA.-CAROTENE 1000 [iU]/1 1; CALCIUM ASCORBATE 100 mg/1 1; CHOLECALCIFEROL 400 [iU]/1 1; .ALPHA.-TOCOPHEROL ACETATE, DL- 30 [iU]/1 1; THIAMINE MONONITRATE 3 mg/1 1; RIBOFLAVIN 3 mg/1 1; NIACINAMIDE 15 mg/1 1; PYRIDOXINE HYDROCHLORIDE 20 mg/1 1; CYANOCOBALAMIN 12 ug/1 1; CALCIUM PANTOTHENATE 7 mg/1 1; CALCIUM CARBONATE 200 mg/1 1; FERROUS FUMARATE 29 mg/1 1; ZINC OXIDE 20 mg/1 1
INACTIVE INGREDIENTS: ACACIA; SILICON DIOXIDE; MAGNESIUM STEARATE; ORANGE JUICE; STEARIC ACID; STEVIA REBAUDIUNA LEAF; SUCROSE

Se-Natal 19 Chewable Tablets

A Prescription Prenatal Vitamin with other Vitamins and Minerals for Nutritional Supplementation

Rx Only

DESCRIPTION

Se·Natal 19 Chewable tablets are round, debossed "TL015." These tablets provide oil-soluble vitamins, water-soluble vitamins and minerals. Each tablet contains:

Supplement Facts
Servings per Bottle: | 100 | %DV For Pregnant and Lactating Women
Serving Size | 1 chewable tablet
Each Tablet contains:
Vitamin A (as beta carotene) | 1000 IU | 23%
Vitamin C (calcium ascorbate) | 100 mg | 83%
Vitamin D (as cholecalciferol) | 10 mcg | 67%
Vitamin E (as dl-alpha tocopherol acetate) | 30 IU | 142%
Thiamine (Vitamin B1) | 3 mg | 214%
Riboflavin (Vitamin B2) | 3 mg | 188%
Niacin (as niacinamide) | 15 mg | 83%
Vitamin B6 (as pyridoxine HCl) | 20 mg | 1000%
Folate (folic acid) | 1000 mcg | 167%
Vitamin B12 (as cyanocobalamin) | 12 mcg | 429%
Pantothenic Aicd (as calcium pantothenate) | 7 mg | 100%
Calcium (as calcium carbonate) | 200 mg | 15%
Iron (as ferrous fumarate) | 29 mg | 107%
Zinc (as zinc oxide) | 20 mg | 154%

CLINICAL PHARMACOLOGY

Oral iron is absorbed most efficiently when administered between meals. Iron is critical for normal hemogloblin syntheis to maintain oxygen transport, energy production and proper function of cells. Adequate amounts of iron are necessary for effective erythropoiesis. Iron also serves as a cofactor of several essential enzymes, including cytochromes, which are involved in electron transport. Folic acid is required for nucleoprotein synthesis and the maintenance of normal erythropoiesis. Folic acid is the precursor of tetrahydrofolic acid, which is involved as a cofactor for transformylation reactions in the biosynthesis of purines and thymidylates of nucleic acids. Deficiency of folic acid may account for the defective deoxyribonucleic acid (DNA) synthesis that leads to megaloblast formation and megablastic macrocytic anemias. Vitamin B12 is essential to growth cell reproduction, hematopoiesis, nucleic acid, and myelin synthesis. Deficiency may result in megaloblastic anemia or pernicious anemia.

OTHER INGREDIENTS

Acacia, Fumed Silica, Magnesium Stearate, Natural Orange Flavour, Orange Juice Powder, Stearic Acid, Stevia, Sucrose.

INDICATIONS AND USAGE

Se-Natal 19 Chewable Tablets are indicated for use in improving the nutritional status of women throughout pregnancy and in the postnatal period for both lactating and non-lactating mothers. Se-Natal 19 Chewable Tablets are also useful in improving the nutritional status of women prior to conception.

CONTRAINDICATIONS

This product is contraindicated in patients with a known hypersensitivity to any of the ingredients.

WARNINGS

Folic acid alone is improper therapy in the treatment of pernicious anemia and other megaloblastic anemias where vitamin B12 is deficient.

BOXED WARNING

WARNING: Accidental overdose of iron-containing products is a leading cause of fatal poisoning in children under 6. Keep this product out of reach of children. In case of accidental overdose, call a doctor or poison control center immediately.

PRECAUTIONS

GENERAL

Take 2 hours after meals. Do not exceed recommended dose. Discontinue use if symptoms of intolerance appear.

Folic Acid

Folic acid in doses above 0.1 mg daily may obscure pernicious anemia. In that hematologic remission can occur while neurological manifestations remain progressive.

Pediatric Use

Safety and effectiveness in pediatric patients have not been established.

Geriatric Use

Dosing for elderly patients should be cautious. Due to the greater frequency of decreased hepatic, renal, or cardiac function, and of concomitant disease or other drug therapy, dosing should start at the lower end of the dosing range.

ADVERSE REACTIONS

Adverse reactions with iron therapy may include GI irritation, constipation, diarrhea, nausea, vomiting, and dark stools. Adverse reactions with iron therapy are usually transient. Allergic sensitization has been reported following both oral and parenteral administration of folic acid.

DRUG INTERACTIONS

Prescriber should be aware of a number of iron/drug interactions, including antacids, tetracyclines, or fluoroquinolones.

OVERDOSAGE

Symptoms:

Abdominal pain, metabolic acidosis, anuria, CNS damage, coma, convulsions, death, dehydration, diffuse vascular congestion, hepatic cirrhosis, hypotension, hypothermia, lethargy, nausea, vomiting, diarrhea, tarry stools, melena, hematemesis, tachycardia, hyperglycemia, drowsiness, pallor, cyanosis, lassitude, seizures, and shock.

DOSAGE AND ADMINISTRATION

One tablet daily, or as directed by a physician.

NOTICE

Contact with moisture can discolor or erode the tablet.

HOW SUPPLIED

Se-Natal 19 Chewable Tablets for oral administration are supplied as multi-color-speckled, round tablets debossed "TL015," packaged in bottles of 100 tablets.

Product Code: 13925-117-01

STORAGE

Store at 20°-25°C (68°-77°F), excursions permitted to 15°-30°C (59°-86°F)[See USP controlled room temperature].

PHARMACIST

Dispense in a tight, light-resistant container as defined in the USP/INF with child-resistant closure.

Call your doctor about side effects. You may report side effects to FDA at 1-800-FDA-1088.

Reserved for Professional

Recommendation.

KEEP THIS AND ALL DRUGS OUT OF THE REACH OF CHILDREN.

Rx Only

Manufactured For:
Seton Pharmaceuticals
Manasquan, NJ 08736
1-800-510-3401
MADE IN CANADA

Code 640138

Rev. 03/24

SETON PHARMACEUTICALS

PACKAGE LABEL.PRINCIPAL DISPLAY PANEL

NDC 13925-117-01

Se-Natal 19 Chewable Tablets

A Prescription Prenatal Vitamin with other Vitamins and Minerals for Nutritional Supplementation

Rx Only

100 Tablets

SETON
PHARMACEUTICALS